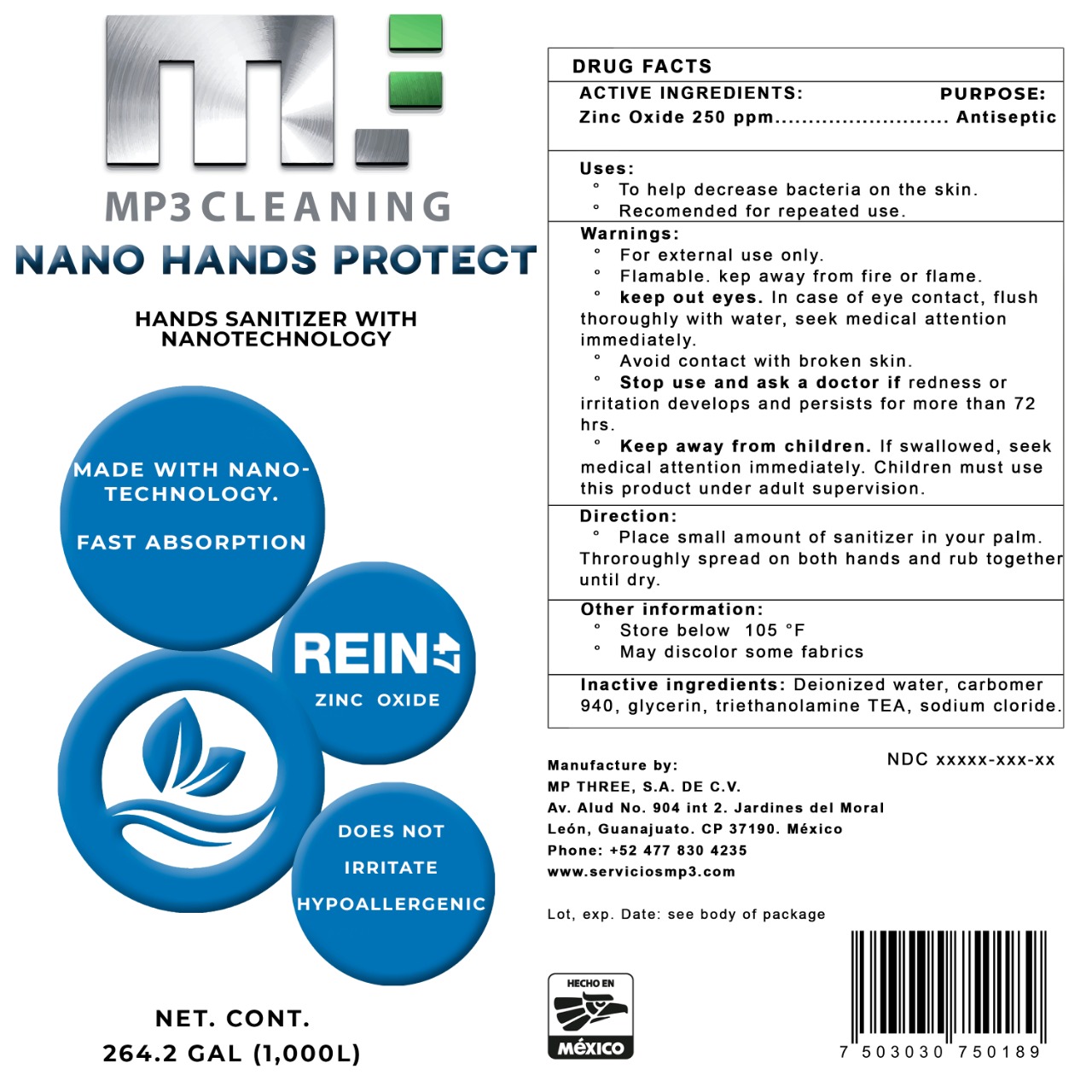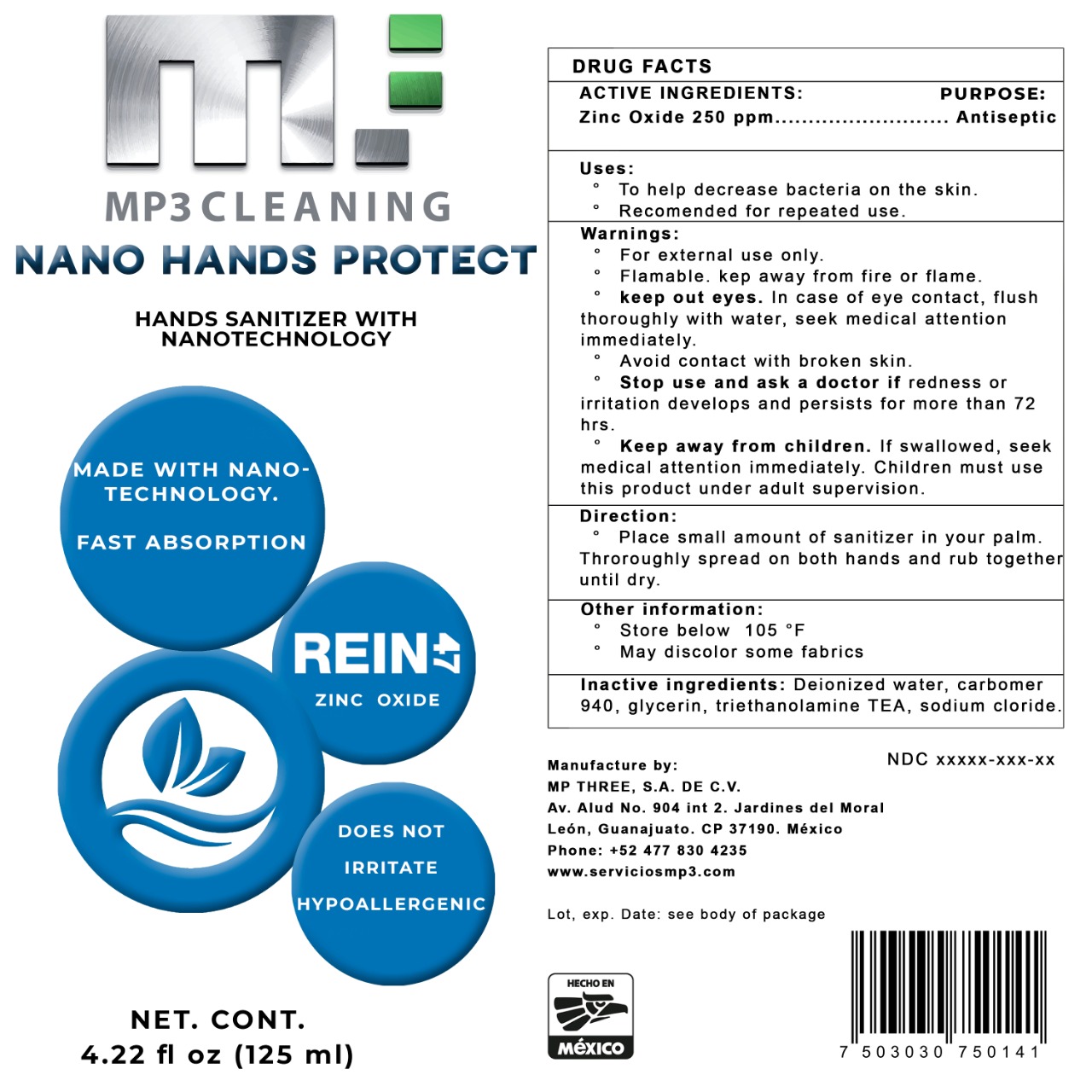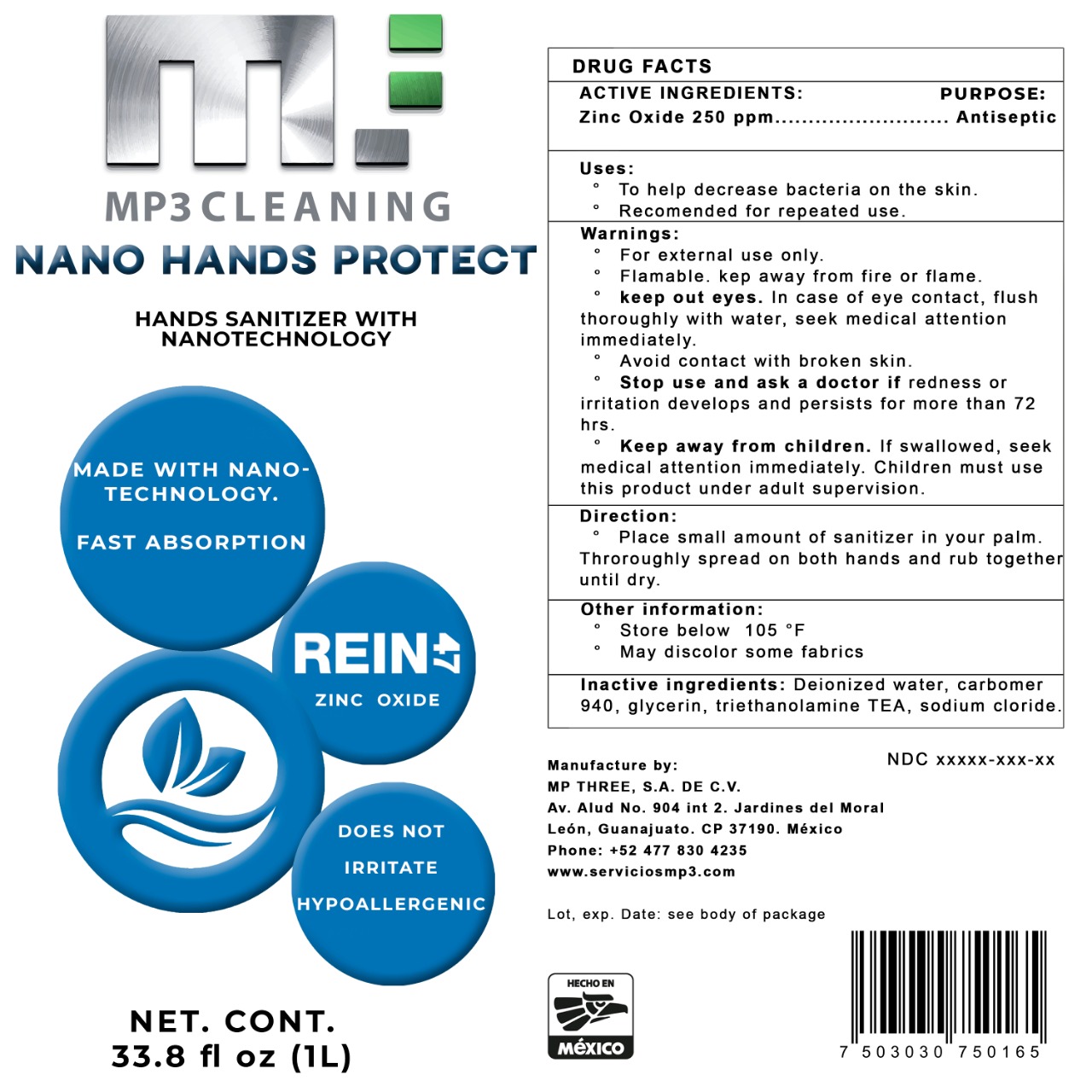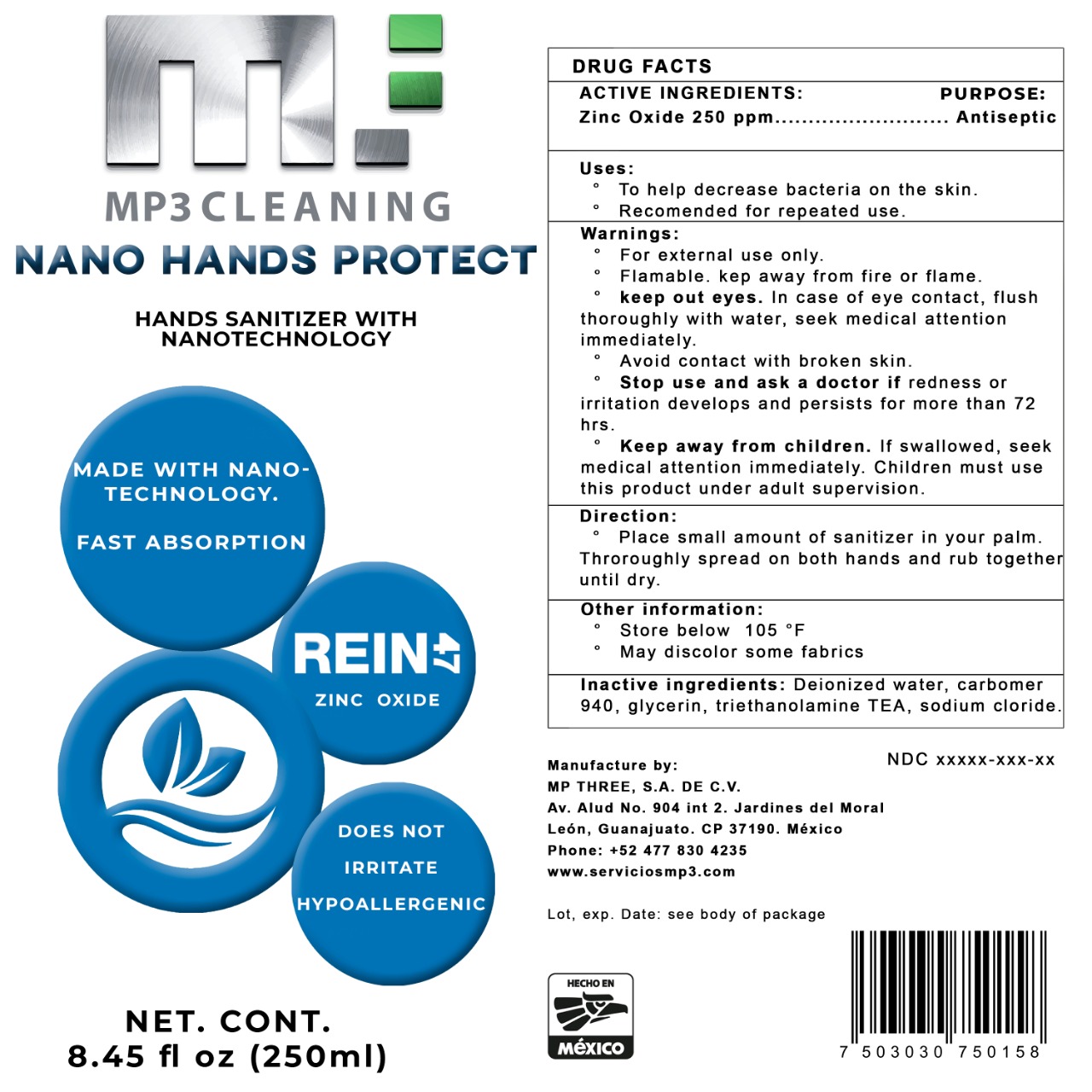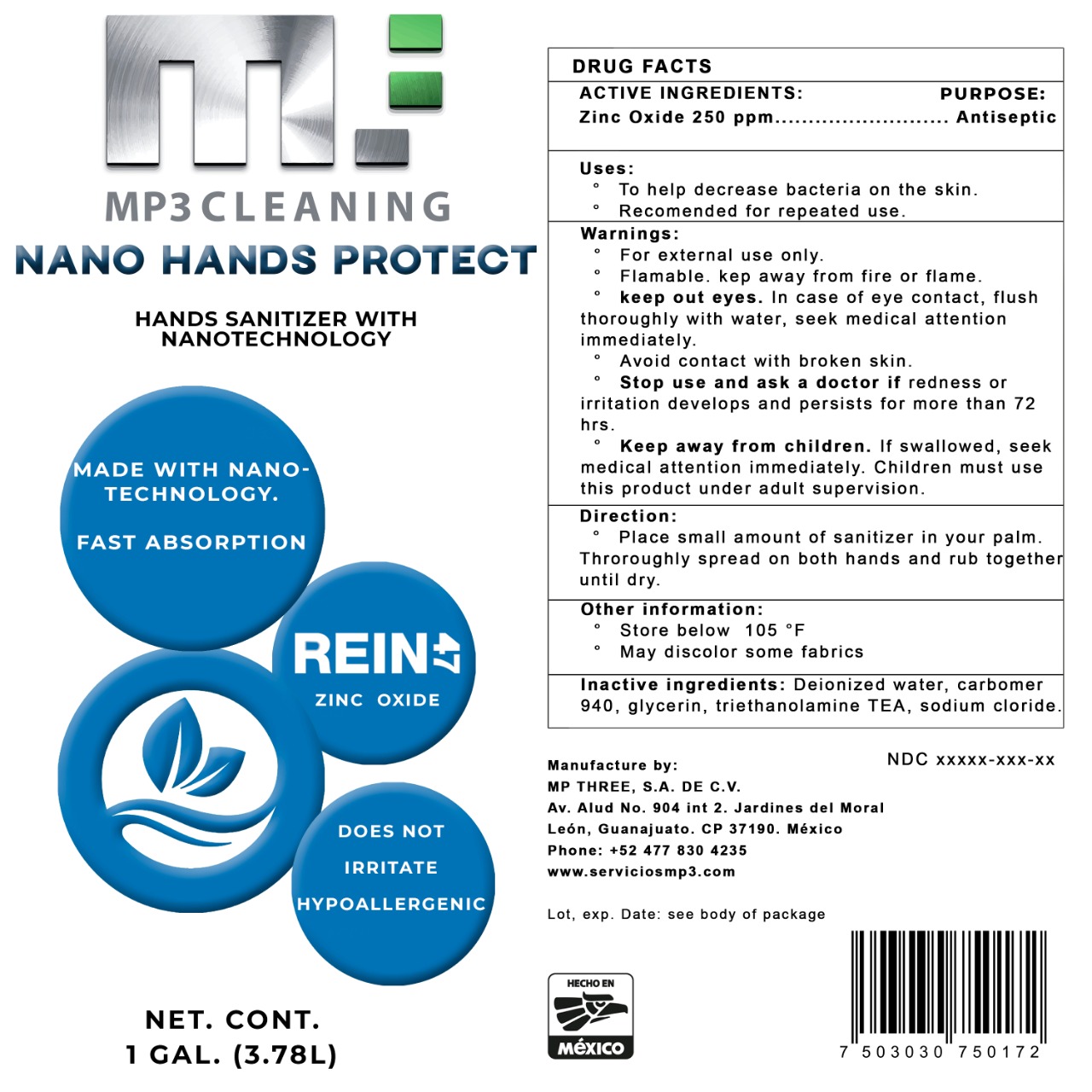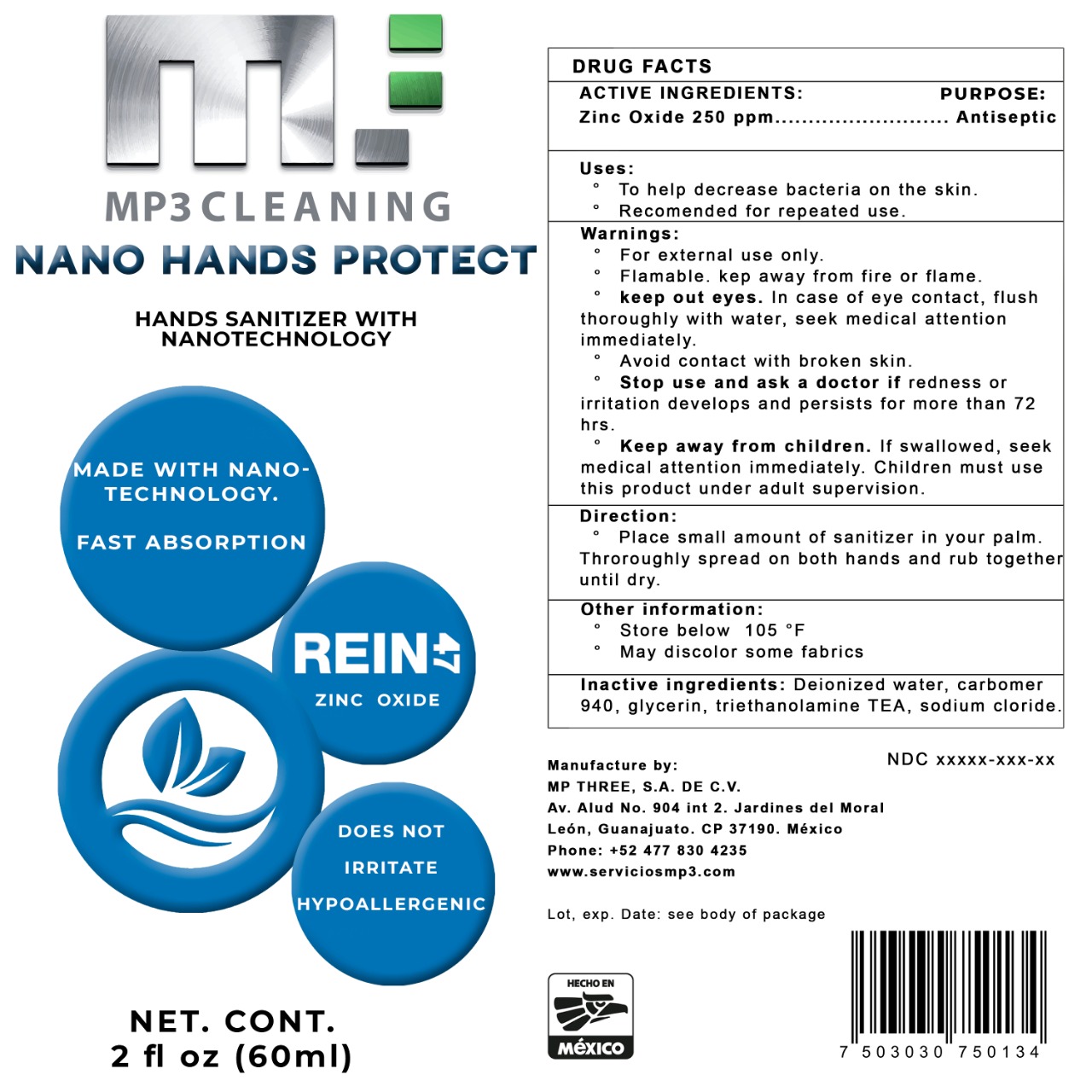 DRUG LABEL: Hand Sanitizer
NDC: 79528-003 | Form: GEL
Manufacturer: Mp Three, S.A. de C.V.
Category: otc | Type: HUMAN OTC DRUG LABEL
Date: 20200710

ACTIVE INGREDIENTS: ZINC OXIDE 0.025 mg/100 mL
INACTIVE INGREDIENTS: SEA SALT; GLYCERIN; TRIETHANOLAMINE TRIS(DIHYDROGEN PHOSPHATE); WATER; CARBOMER 940

HAND SANITIZER

This is a hand sanitizer manufactured according to the Temporary Policy for Preparation of Certain Alcohol-Based Hand Sanitizer Products During the Public Health Emergency (CoViD-19); Guidance for Industry.

The hand sanitizer is manufactured using only the following United States Pharmacopoeia (USP) grade ingredients in the preparation of the product (percentage in final product formulation) consistent with World Health Organization (WHO) recommendations:

1. Zinc Oxide (0.025%, v/v) in an aqueous solution denatured according to Alcohol and Tobacco Tax and Trade Bureau regulations in 27 CFR part 20.
2. Sterile distilled water or boiled cold water.
3. Carbomer 940
4. Glycerin
5. Triethanolamine
6. Sodium Cloride

The firm does not add other active or inactive ingredients. Different or additional ingredients may impact the quality and potency of the product.

Active Ingredient(s)

Zinc Oxide 0.025% v/v. Purpose: Antiseptic

Purpose

Antiseptic, Hand Sanitizer

Use

Hand Sanitizer to help reduce bacteria that potentially can cause disease. For use when soap and water are not available.

Warnings

For external use only. Flammable. Keep away from heat or flame

Do not use

- in children less than 2 months of age
- on open skin wounds

When using this product keep out of eyes, ears, and mouth. In case of contact with eyes, rinse eyes thoroughly with water.
Stop use and ask a doctor if irritation or rash occurs. These may be signs of a serious condition.
Keep out of reach of children. If swallowed, get medical help or contact a Poison Control Center right away.

Stop use and ask a doctor if irritation or rash occurs. These may be signs of a serious condition.

Keep out of reach of children. If swallowed, get medical help or contact a Poison Control Center right away.

Directions

- Place enough product on hands to cover all surfaces. Rub hands together until dry.
- Supervise children under 6 years of age when using this product to avoid swallowing.

Other information

- Store between 15-30C (59-86F)
- Avoid freezing and excessive heat above 40C (104F)

Inactive ingredients

Deionized water, carbomer 940, glycerin, triethanolamine, sodium cloride

Package Label - Principal Display Panel

1000 ml NDC: 79528-003-01

3780 ml NDC: 79528-003-02

60 ml NDC: 79528-003-03

125 ml NDC: 79528-003-04

250 ml NDC: 79528-003-05

1000000 ml NDC: 79528-003-06